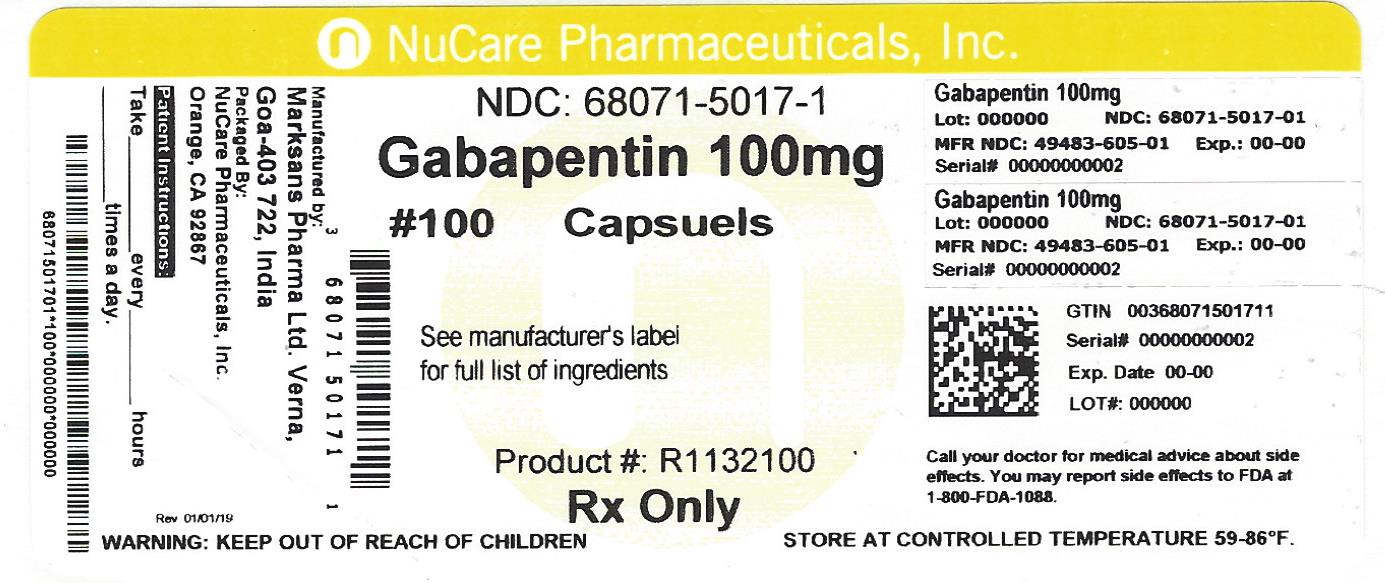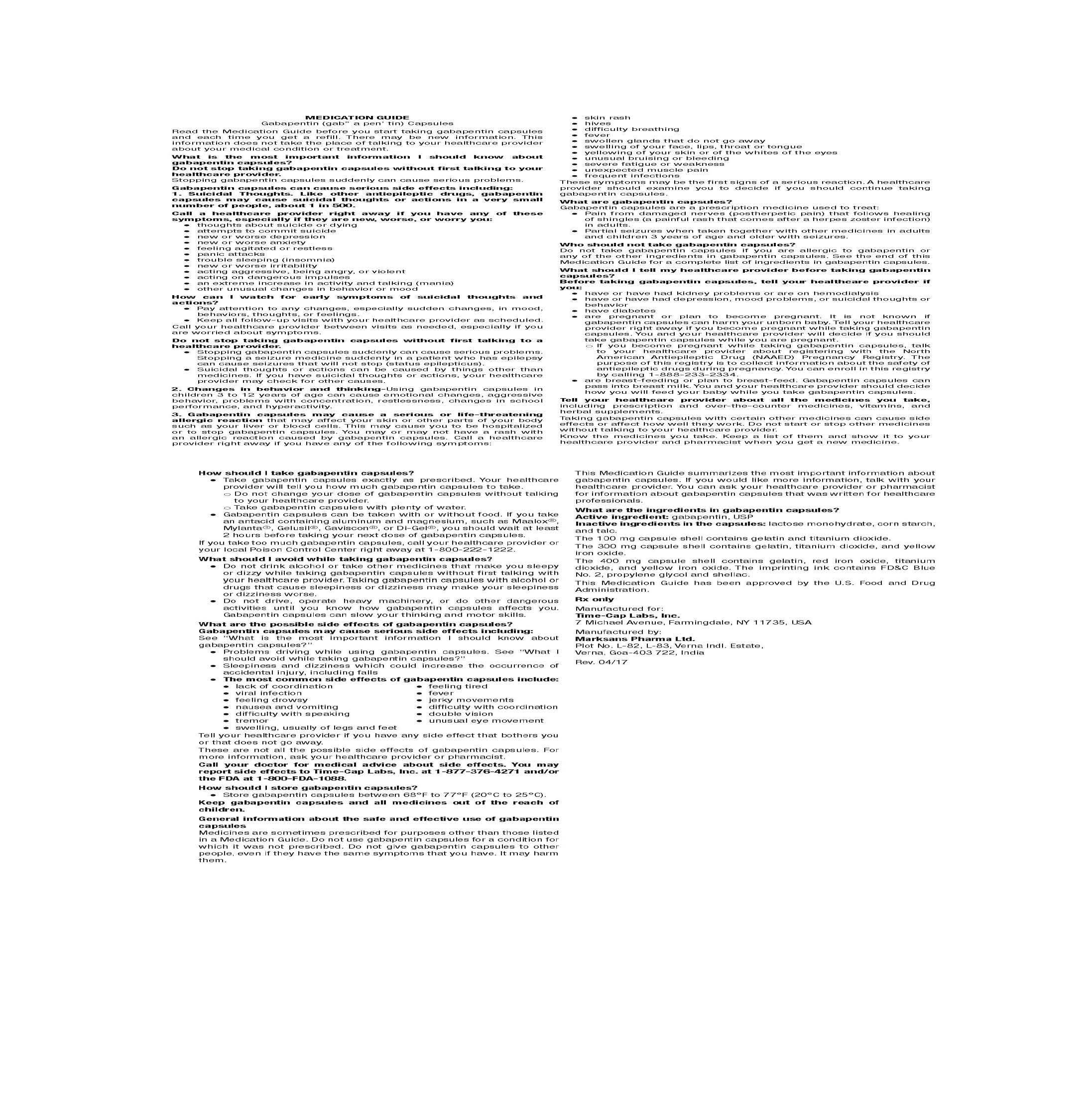 DRUG LABEL: GABAPENTIN
NDC: 68071-5017 | Form: CAPSULE
Manufacturer: NuCare Pharmaceuticals,Inc.
Category: prescription | Type: HUMAN PRESCRIPTION DRUG LABEL
Date: 20240619

ACTIVE INGREDIENTS: GABAPENTIN 100 mg/1 1
INACTIVE INGREDIENTS: LACTOSE MONOHYDRATE; STARCH, CORN; TALC; GELATIN; TITANIUM DIOXIDE; FD&C BLUE NO. 2; PROPYLENE GLYCOL; SHELLAC

HOW SUPPLIED

100 mg Capsules (White/White colored, size 3 hard gelatin capsules with 103 printed on body of capsules containing white to off white granular powder)

NDC 68071-5017-1 BOTTLES OF 100